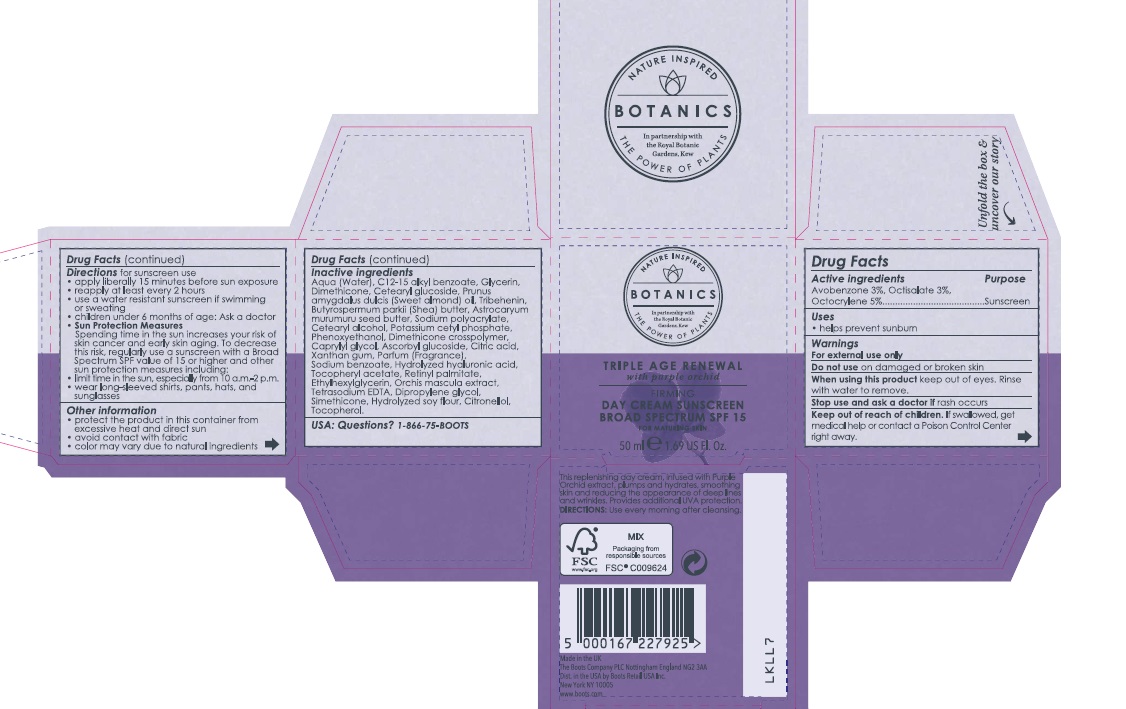 DRUG LABEL: Botanics Triple Age Renewal Day Cream Sunscreen Broad Spectrum SPF 15
NDC: 11489-095 | Form: CREAM
Manufacturer: BCM Ltd
Category: otc | Type: HUMAN OTC DRUG LABEL
Date: 20170614

ACTIVE INGREDIENTS: AVOBENZONE 1.5 g/50 g; OCTISALATE 1.5 g/50 g; OCTOCRYLENE 2.5 g/50 g
INACTIVE INGREDIENTS: WATER; ALKYL (C12-15) BENZOATE; GLYCERIN; DIMETHICONE; CETEARYL GLUCOSIDE; ALMOND OIL; TRIBEHENIN; ASTROCARYUM MURUMURU SEED BUTTER; SHEA BUTTER; SODIUM POLYACRYLATE (8000 MW); CETOSTEARYL ALCOHOL; POTASSIUM CETYL PHOSPHATE; PHENOXYETHANOL; CAPRYLYL GLYCOL; ASCORBYL GLUCOSIDE; CITRIC ACID MONOHYDRATE; XANTHAN GUM; SODIUM BENZOATE; .ALPHA.-TOCOPHEROL ACETATE; VITAMIN A PALMITATE; ETHYLHEXYLGLYCERIN; ORCHIS MASCULA WHOLE; EDETATE SODIUM; DIPROPYLENE GLYCOL; SILICON DIOXIDE; TOCOPHEROL

Carton Active Ingredients Section

Active Ingredients

Avobenzone 3%

Octisalate 3%

Octocrylene 5%

Purpose Sunscreen

Uses

Uses - helps prevent sunburn.

Warnings

For external use only

Do not use on damaged or broken skin

When using this product keep out of eyes. Rinse with water to remove

Ask a doctor

Stop use and ask a doctor if rash occurs.

Keep out of reach of children. If swallowed, get medical help or contact a Poison Centre right away.

Directions

Directions for sunscreen use

apply liberally 15 minutes before sun exposure

reapply at least every 2 hours

use a water resistant sunscreen if swimming or sweating

children under 6 months of age: Ask a doctor

Sun Protection Measures. Spending time in the sun increases your risk of skin cancer and early skin aging. To decrease this risk, regularly use a sunscreen with a Broad Spectrum SPF value of 15 or higher and other sun protection measures including:

limit time in the sun, especially from 10 a.m. – 2 p.m.

wear long-sleeved shirts, pants, hats, and sunglasses

Storage

Other information - protect the product in this container from excessive heat and direct sun

Inactive ingredients

Aqua (Water), C12-15 alkyl benzoate, Glycerin, Dimethicone, Cetearyl glucoside, Prunus amygdalus dulcis (Sweet almond) oil, Tribehenin, Astrocaryum murumuru butter, Butyrospermum parkii (Shea) butter, Sodium polyacrylate, Cetearyl alcohol, Potassium cetyl phosphate, Phenoxyethanol, Dimethicone crosspolymer, Caprylyl glycol, Ascorbyl glucoside, Citric acid, Xanthan gum, Parfum (Fragrance), Sodium benzoate, Hydrolyzed hyaluronic acid, Tocopheryl acetate, Retinyl palmitate, Ethylhexylglycerin, Orchis mascula extract, Tetrasodium EDTA, Dipropylene glycol, Glycine soja (soyabean) protein, Citronellol, Silica, Tocopherol

Description

Firms, lifts and reduces the appearance of deep lines and wrinkles.

Active plant extract, Purple Orchid contains anti-oxidants and polysaccharides to help protect and smooth the skin.

Directions: Use every morning after cleansing. Colour may vary due to natural ingredients. Formulated without parabens.

Information

Made in the UK.

The Boots Company PLC Nottingham England NG2 3AA

Dist. in the USA by Boots Retain USA Inc. Norwalk CT 06851 USA

www.boots.com

Jar label

Boots Botanics The Power of Plants

Day Cream Sunscreen Broad Spectrum SPF 15

50ml e 1.69 US Fl. Oz.

Active ingredients: Avobenzone 3%, Octisalate 3%, Octocrylene 5%

Warnings

Avoid contact with eyes. If product gets into the eyes, rinse well with water immediately.

Description

Directions: Use every morning after cleansing

Information

The Boots Company PLC

Notingham England NG2 3AA

Dist. in the USA by Boots Retail USA Inc. Norwalk CT 06851 USA

Made in the UK

www.boots.com

PACKAGE LABEL

carton